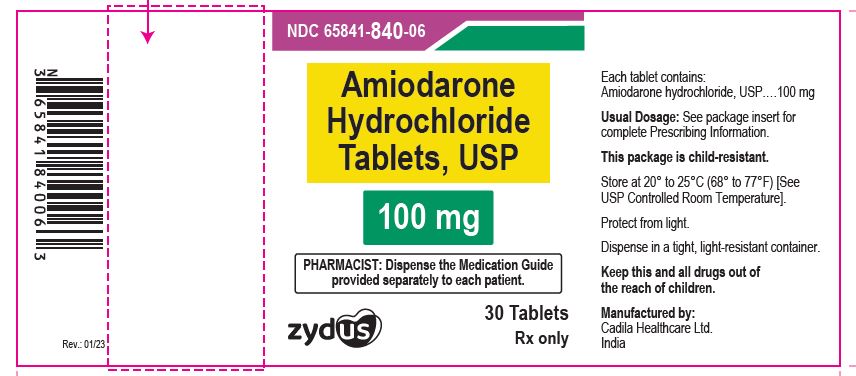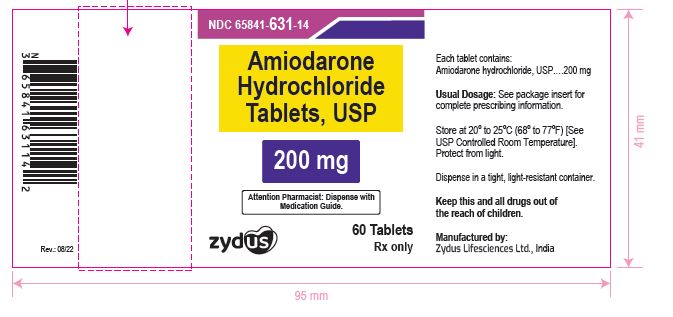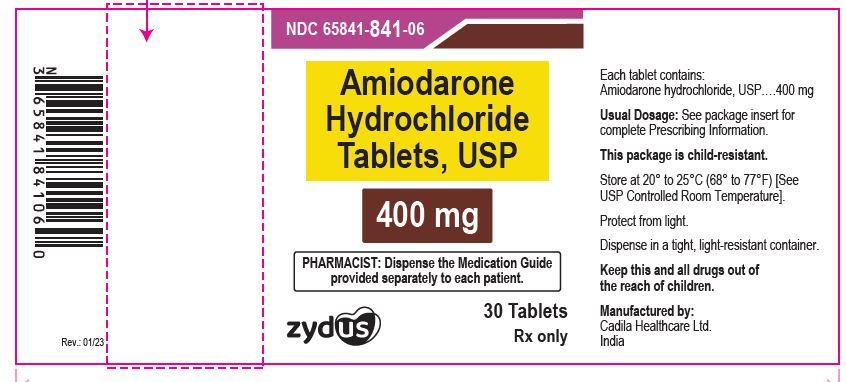 DRUG LABEL: Amiodarone hydrochloride
NDC: 65841-840 | Form: TABLET
Manufacturer: Zydus Lifesciences Limited
Category: prescription | Type: HUMAN PRESCRIPTION DRUG LABEL
Date: 20241125

ACTIVE INGREDIENTS: AMIODARONE HYDROCHLORIDE 100 mg/1 1
INACTIVE INGREDIENTS: LACTOSE MONOHYDRATE; MAGNESIUM STEARATE; SILICON DIOXIDE; SODIUM STARCH GLYCOLATE TYPE A POTATO; POVIDONE; STARCH, CORN

AMIODARONE HYDROCHLORIDE TABLETS

PACKAGE LABEL.PRINCIPAL DISPLAY PANEL

NDC 65841-840-06

Amiodarone Hydrochloride Tablets USP, 100 mg

30 Tablets

Rx only

NDC 65841-631-14 in bottle of 60 tablets

Amiodarone Hydrochloride Tablets, 200 mg

Rx only

NDC 65841-841-06

Amiodarone Hydrochloride Tablets USP, 400 mg

30 Tablets

Rx only